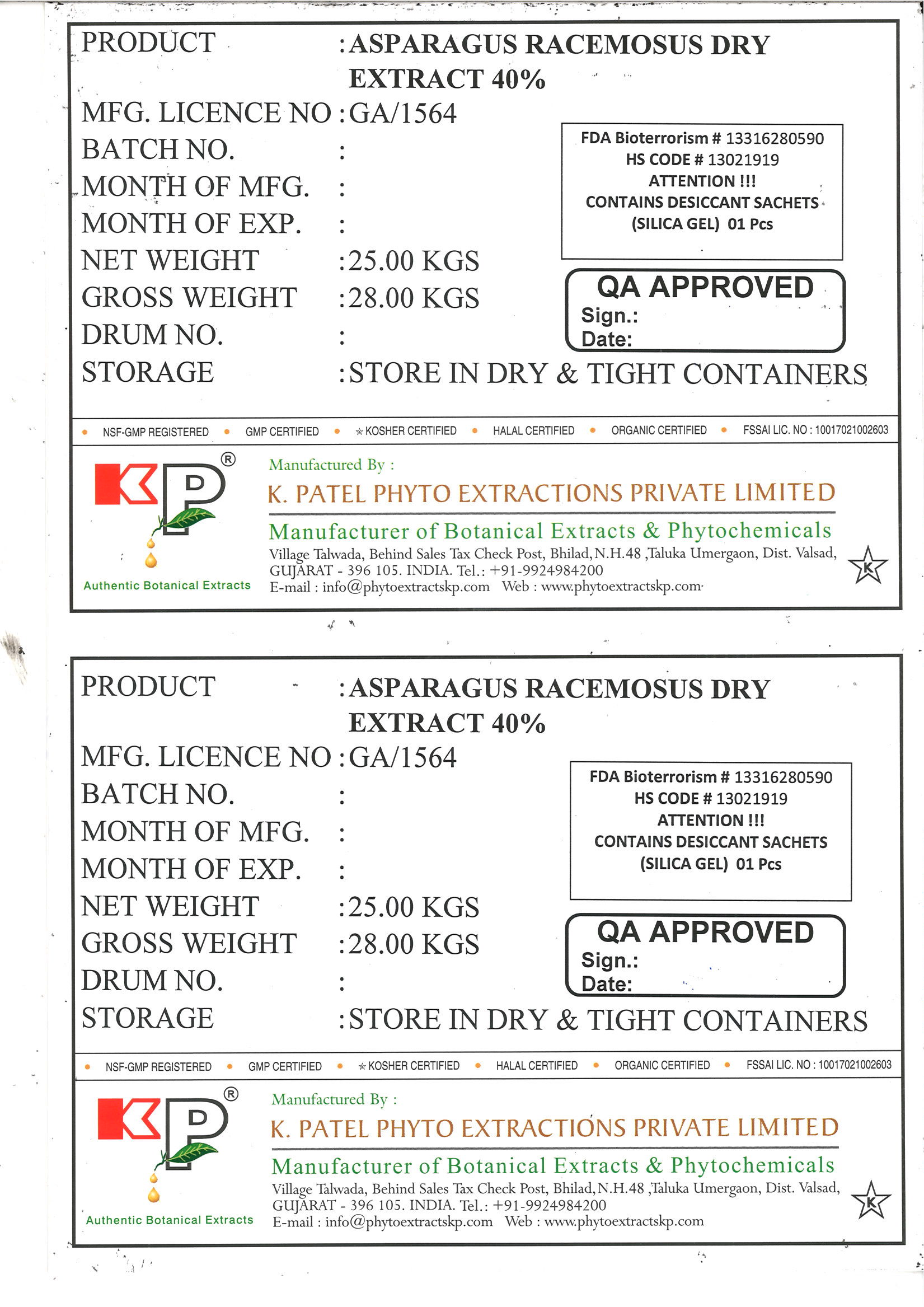 DRUG LABEL: Asparagus racemosus dry extract 40%
NDC: 73276-004 | Form: POWDER
Manufacturer: K. Patel Phyto Extractions Private Limited
Category: other | Type: BULK INGREDIENT
Date: 20250625

ACTIVE INGREDIENTS: ASPARAGUS RACEMOSUS ROOT 25 kg/25 kg

Asparagus racemosus dry extract 40%